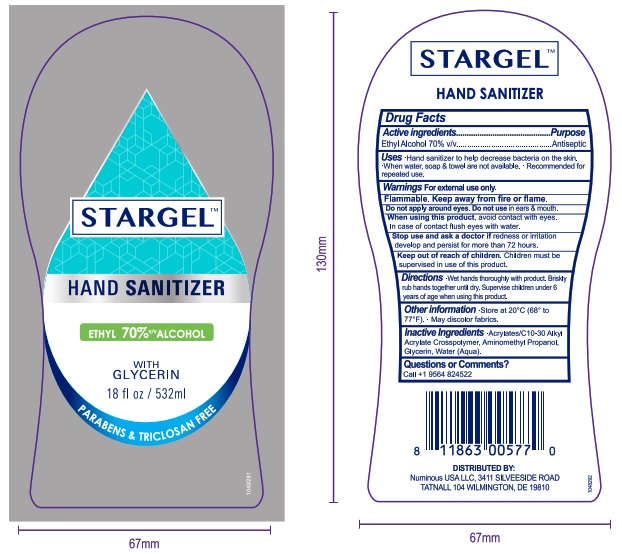 DRUG LABEL: STARGEL
NDC: 80061-001 | Form: GEL
Manufacturer: J Plus Cosmética, S.A. de C.V.				
Category: otc | Type: HUMAN OTC DRUG LABEL
Date: 20201231

ACTIVE INGREDIENTS: ALCOHOL 70 mL/100 mL
INACTIVE INGREDIENTS: GLYCERIN 0.2 mL/100 mL; AMINOMETHYLPROPANOL 0.2 mL/100 mL; WATER; CARBOMER 1342 0.5 mL/100 mL

Purpose

Antiseptic, Hand Sanitizer

Use

Hand Sanitizer to help reduce bacteria that potentially can cause disease. For use when soap, water and towel are not available.

Recomended for repeated use.

Warnings

For external use only. Flammable. Keep away from heat or flame

Do not use

- in children less than 2 months of age
- on open skin wounds

When using this product keep out of eyes, ears, and mouth. In case of contact with eyes, rinse eyes thoroughly with water.
Stop use and ask a doctor if irritation or rash occurs. These may be signs of a serious condition.
Keep out of reach of children. If swallowed, get medical help or contact a Poison Control Center right away.

Stop use and ask a doctor if irritation or rash occurs. These may be signs of a serious condition.

Keep out of reach of children. If swallowed, get medical help or contact a Poison Control Center right away.

Directions

- Place enough product on hands to cover all surfaces. Rub hands together until dry.
- Supervise children under 6 years of age when using this product to avoid swallowing.

Other information

- Store between 15-30C (59-86F)
- Avoid freezing and excessive heat above 40C (104F)

Inactive ingredients

Aminomethylpropanol, carbomer 1342, glycerin, water (aqua)

Active ingredient

Alcohol 70% Purpose: Antiseptic

Package Label - Principal Display Panel

532 mL NDC: 80061-001-01